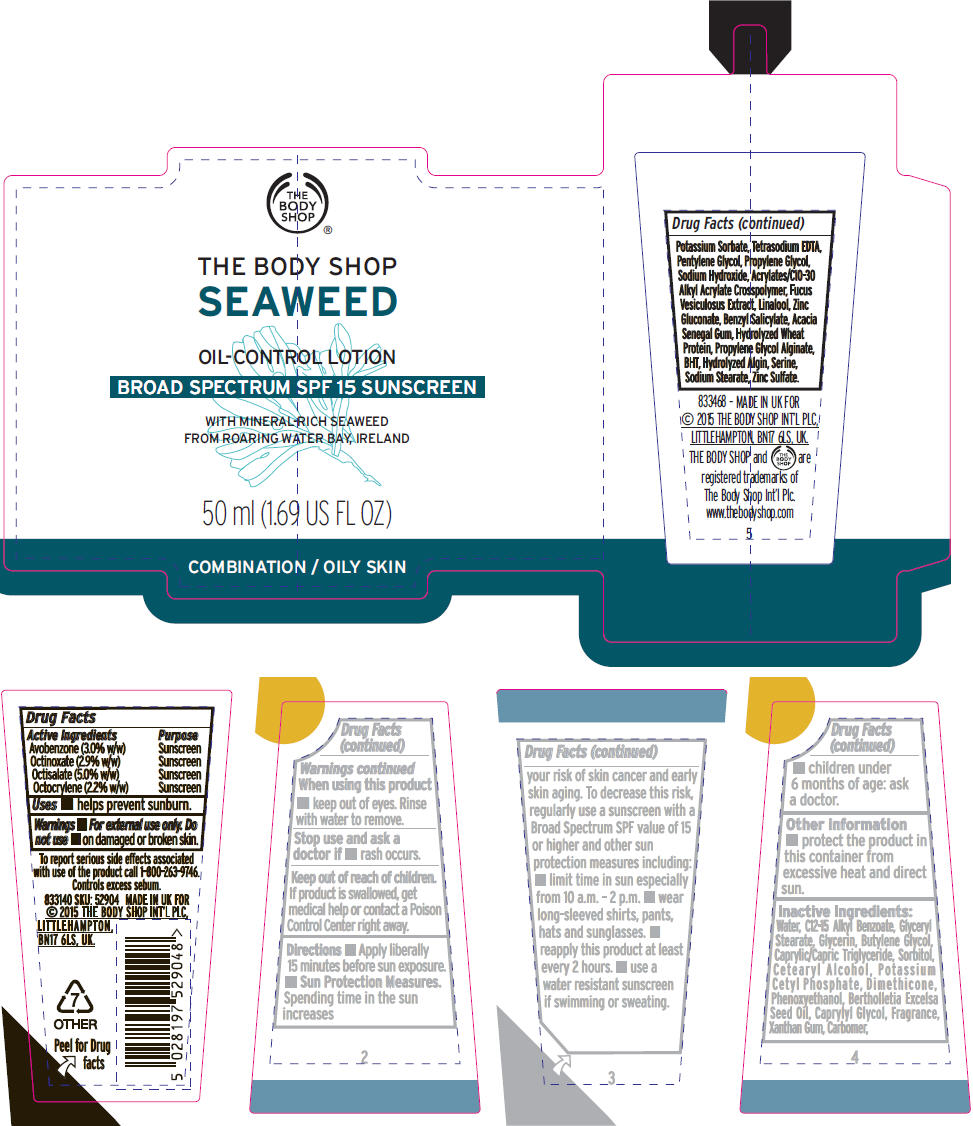 DRUG LABEL: Seaweed Oil-Control SPF 15
NDC: 57691-904 | Form: LOTION
Manufacturer: Buth-Na-Bodhaige, Inc.,
Category: otc | Type: HUMAN OTC DRUG LABEL
Date: 20161010

ACTIVE INGREDIENTS: Octisalate 0.05 g/1 mL; Avobenzone 0.03 g/1 mL; Octinoxate 0.029 g/1 mL; Octocrylene 0.022 g/1 mL
INACTIVE INGREDIENTS: Water; Alkyl (C12-15) Benzoate; GLYCERYL MONOSTEARATE; Glycerin; Butylene Glycol; MEDIUM-CHAIN TRIGLYCERIDES; Sorbitol; Cetostearyl Alcohol; Potassium Cetyl Phosphate; Dimethicone; Phenoxyethanol; BRAZIL NUT OIL; Caprylyl Glycol; Xanthan Gum; Carboxypolymethylene; Potassium Sorbate; Edetate Sodium; Pentylene Glycol; Propylene Glycol; Sodium Hydroxide; CARBOMER INTERPOLYMER TYPE A (ALLYL SUCROSE CROSSLINKED); FUCUS VESICULOSUS; LINALOOL, (+/-)-; Zinc Gluconate; Benzyl Salicylate; ACACIA; HYDROLYZED WHEAT PROTEIN (ENZYMATIC; 3000 MW); Propylene Glycol Alginate; BUTYLATED HYDROXYTOLUENE; Serine; Sodium Stearate; Zinc Sulfate, Unspecified Form; SODIUM ALGINATE

Seaweed Oil-Control Lotion SPF 15

Drug Facts

ACTIVE INGREDIENT

Active Ingredients | Purpose
Avobenzone (3.0% w/w) | Sunscreen
Octinoxate (2.9% w/w) | Sunscreen
Octisalate (5.0% w/w) | Sunscreen
Octocrylene (2.2% w/w) | Sunscreen

Uses

- helps prevent sunburn.

Warnings

- For external use only.

Do not use

- on damaged or broken skin.

When using this product

- keep out of eyes. Rinse with water to remove.

Stop use and ask a doctor if

- rash occurs.

Keep out of reach of children.

If product is swallowed, get medical help or contact a Poison Control Center right away.

Directions

- Apply liberally 15 minutes before sun exposure.
- Sun Protection Measures. Spending time in the sun increases your risk of skin cancer and early skin aging. To decrease this risk, regularly use a sunscreen with a Broad Spectrum SPF value of 15 or higher and other sun protection measures including:
  - limit time in sun especially from 10 a.m. – 2 p.m.
  - wear long-sleeved shirts, pants, hats and sunglasses.
  - reapply this product at least every 2 hours.
  - use a water resistant sunscreen if swimming or sweating.
- children under 6 months of age: ask a doctor.

Other information

- protect the product in this container from excessive heat and direct sun.

Inactive Ingredients

Water, C12-15 Alkyl Benzoate, Glyceryl Stearate, Glycerin, Butylene Glycol, Caprylic/Capric Triglyceride, Sorbitol, Cetearyl Alcohol, Potassium Cetyl Phosphate, Dimethicone, Phenoxyethanol, Bertholletia Excelsa Seed Oil, Caprylyl Glycol, Fragrance, Xanthan Gum, Carbomer, Potassium Sorbate, Tetrasodium EDTA, Pentylene Glycol, Propylene Glycol, Sodium Hydroxide, Acrylates/C10-30 Alkyl Acrylate Crosspolymer, Fucus Vesiculosus Extract, Linalool, Zinc Gluconate, Benzyl Salicylate, Acacia Senegal Gum, Hydrolyzed Wheat Protein, Propylene Glycol Alginate, BHT, Hydrolyzed Algin, Serine, Sodium Stearate, Zinc Sulfate.

PRINCIPAL DISPLAY PANEL - 50 ml Tube Label

THE
BODY
SHOP

THE BODY SHOP
SEAWEED

OIL-CONTROL LOTION
BROAD SPECTRUM SPF 15 SUNSCREEN

WITH MINERAL-RICH SEAWEED
FROM ROARING WATER BAY, IRELAND

50 ml (1.69 US FL OZ)

COMBINATION / OILY SKIN